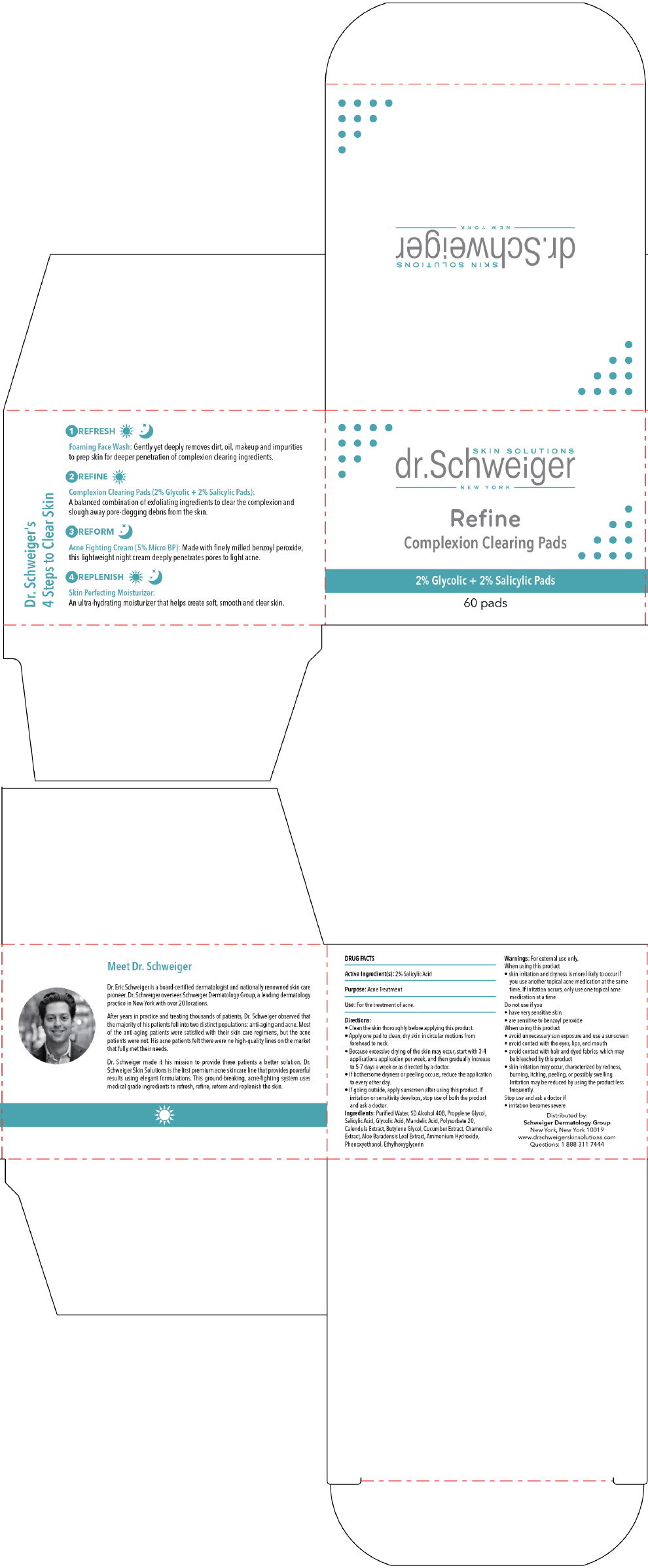 DRUG LABEL: REFINE 
NDC: 70911-110 | Form: SWAB
Manufacturer: SCHWEIGER DERMATOLOGY GROUP
Category: otc | Type: HUMAN OTC DRUG LABEL
Date: 20160915

ACTIVE INGREDIENTS: salicylic acid 20 mg/1 mL
INACTIVE INGREDIENTS: WATER; ALCOHOL; PROPYLENE GLYCOL; GLYCOLIC ACID; MANDELIC ACID; POLYSORBATE 20; calendula officinalis flowering top; BUTYLENE GLYCOL; CHAMOMILE; ALOE VERA LEAF; AMMONIA; PHENOXYETHANOL; ETHYLHEXYLGLYCERIN

REFINE
Complexion Clearing Pads

Drug Facts

Active ingredients

Salicylic Acid 2.00%

Purpose

Acne Treatment

Uses

For the treatment of acne.

Warnings

For External use only.

- When using this product skin irritation and dryness is more likely to occur if you use another topical acne medication at the same time. If irritation occurs, only use one topical acne medication at a time
  Keep out of reach of children
- When using this product, rinse immediately with water if it gets in eyes.
- If swallowed, consult a physician or poison control center.

Directions

- Clean the skin thoroughly before applying this product.
- Cover the entire affected area with a thin layer one to three times daily.
- Because excessive drying of the skin may occur, start with one application daily, then gradually increase to two or three times daily if needed or as directed by a doctor.
- If bothersome dryness or peeling occurs, reduce the application to once a day or every other day.
- If going outside, apply sunscreen after using this product. If irritation or sensitivity develops, stop use of both products and ask a doctor.

Additional Information

Store at room temperature.

Inactive ingredients

Purified Water, SD Alcohol 40B, Propylene Glycol, Salicylic Acid, Glycolic Acid, Mandelic Acid, Polysorbate 20, Calendula Extract, Butylene Glycol, Cucumber Extract, Chamomile Extract, Aloe Baradensis Leaf Extract, Ammonium Hydroxide, Phenoxyethanol, Ethylhexyglycerin.

Questions

1 888 311 7444

Distributed by: Schweiger Dermatology Group
NY, NY 10019

PRINCIPAL DISPLAY PANEL - 60 Pad Carton

SKIN SOLUTIONS
dr.Schweiger
NEW YORK

Refine
Complexion Clearing Pads

2% Glycolic + 2% Salicylic Pads

60 pads